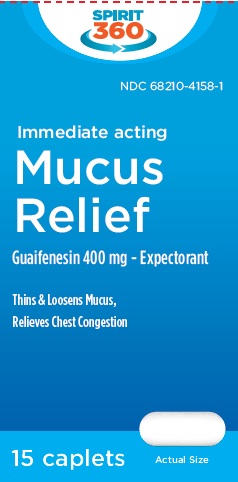 DRUG LABEL: MUCUS RELIEF
NDC: 68210-4158 | Form: TABLET
Manufacturer: Prodose, Inc.
Category: otc | Type: HUMAN OTC DRUG LABEL
Date: 20260126

ACTIVE INGREDIENTS: GUAIFENESIN 400 mg/1 1
INACTIVE INGREDIENTS: SILICON DIOXIDE; MAGNESIUM STEARATE; MALTODEXTRIN; MICROCRYSTALLINE CELLULOSE; POVIDONE K30; SODIUM STARCH GLYCOLATE TYPE A POTATO; STEARIC ACID

MUCUS RELIEF CAPLETS

Active ingredient (in each caplet)

Guaifenesin 400 mg

Purpose

Expectorant

Uses

helps loosen phlegm (mucus) and thin bronchial secretions to rid the bronchial passageways of bothersome mucus and make
coughs more productive

Warnings

Do not use

■ for children under 12 years of age

Ask a doctor before use if you have

■ persistent or chronic cough such as occurs with smoking, asthma, chronic bronchitis, or emphysema
■ cough accompanied by too much phlegm (mucus)

Stop use and ask a doctor if

■ cough lasts more than 7 days, comes back, or occurs with fever, rash, or persistent headache. These could be signs of a
serious condition.

PREGNANCY OR BREAST FEEDING

If pregnant or breast-feeding, ask a health professional before use.

Keep out of reach of children.

In case of overdose, get medical help or contact a Poison Control Center right away. 1-800-222-1222

Directions

■ do not exceed 6 caplets in 24 hours.

■ take with a full glass of water

■ adults and children 12 years of age and over: take 1 caplet every 4 hours with a full glass of water while symptoms
persist.
■ children under 12 years of age: do not use

Other information

■ store between 20-25°C (68-77°F)

Inactive ingredients

colloidal silicon dioxide, magnesium stearate, maltodextrin, microcrystalline cellulose, polyvinyl pyrrolidone, sodium starch
glycolate, stearic acid

Questions or comments?

1-888-333-9792

PRINCIPAL DISPLAY PANEL

Mucus Relief

Guaifenesin 400mg

• Expectorant
• Thins and Loosens Mucus
• Relieves Chest Congestion